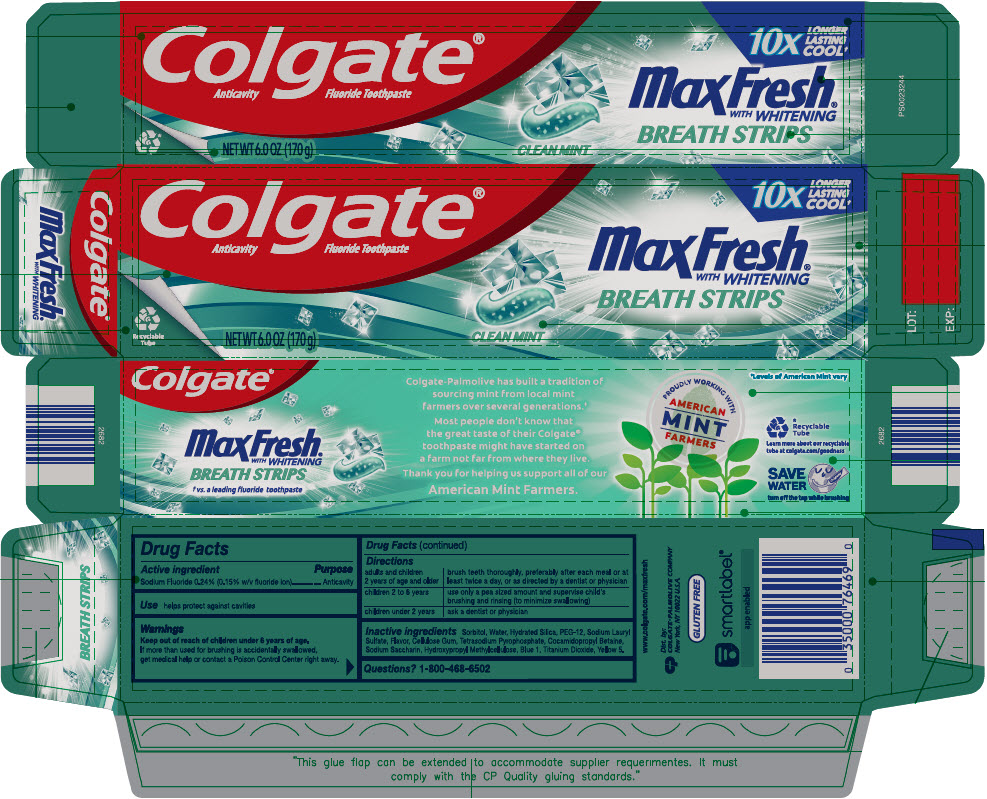 DRUG LABEL: Colgate MaxFresh with Mini Breath Clean Mint
NDC: 35000-013 | Form: PASTE, DENTIFRICE
Manufacturer: Colgate-Palmolive Company
Category: otc | Type: HUMAN OTC DRUG LABEL
Date: 20241114

ACTIVE INGREDIENTS: SODIUM FLUORIDE 1.1 mg/1 g
INACTIVE INGREDIENTS: SORBITOL; WATER; HYDRATED SILICA; POLYETHYLENE GLYCOL 600; SODIUM LAURYL SULFATE; CARBOXYMETHYLCELLULOSE SODIUM, UNSPECIFIED; SODIUM PYROPHOSPHATE; COCAMIDOPROPYL BETAINE; SACCHARIN SODIUM; HYPROMELLOSE, UNSPECIFIED; FD&C BLUE NO. 1; FD&C YELLOW NO. 5; TITANIUM DIOXIDE

Colgateˊ MaxFresh® with Mini Breath Strips Clean Mint

Drug Facts

Active ingredient

Sodium fluoride 0.24% (0.15% w/v fluoride ion)

Purpose

Anticavity

Use

helps protect against cavities

Warnings

Keep out of reach of children under 6 years of age.

If more than used for brushing is accidentally swallowed, get medical help or contact a Poison Control Center right away.

Directions

adults and children 2 years of age and older | brush teeth thoroughly, preferably after each meal or at least twice a day, or as directed by a dentist or physician
children 2 to 6 years | use only a pea sized amount and supervise child's brushing and rinsing (to minimize swallowing)
children under 2 years | ask a dentist or physician

Inactive ingredients

Sorbitol, Water, Hydrated Silica, PEG-12, Sodium Lauryl Sulfate, Flavor, Cellulose Gum, Tetrasodium Pyrophosphate, Cocamidopropyl Betaine, Sodium Saccharin, Hydroxypropyl Methylcellulose, Blue 1, Titanium Dioxide, Yellow 5.

Questions?

1-800-468-6502

Dist. by:
COLGATE-PALMOLIVE COMPANY
New York, NY 10022

PRINCIPAL DISPLAY PANEL - 170 g Tube Carton

Colgate®
Anticavity Fluoride Toothpaste

10X
LONGER
LASTING
COOL†

Max Fresh®
WITH WHITENING

BREATH STRIPS

Recyclable
Tube

NET WT 6.0 OZ (170 g)

CLEAN MINT